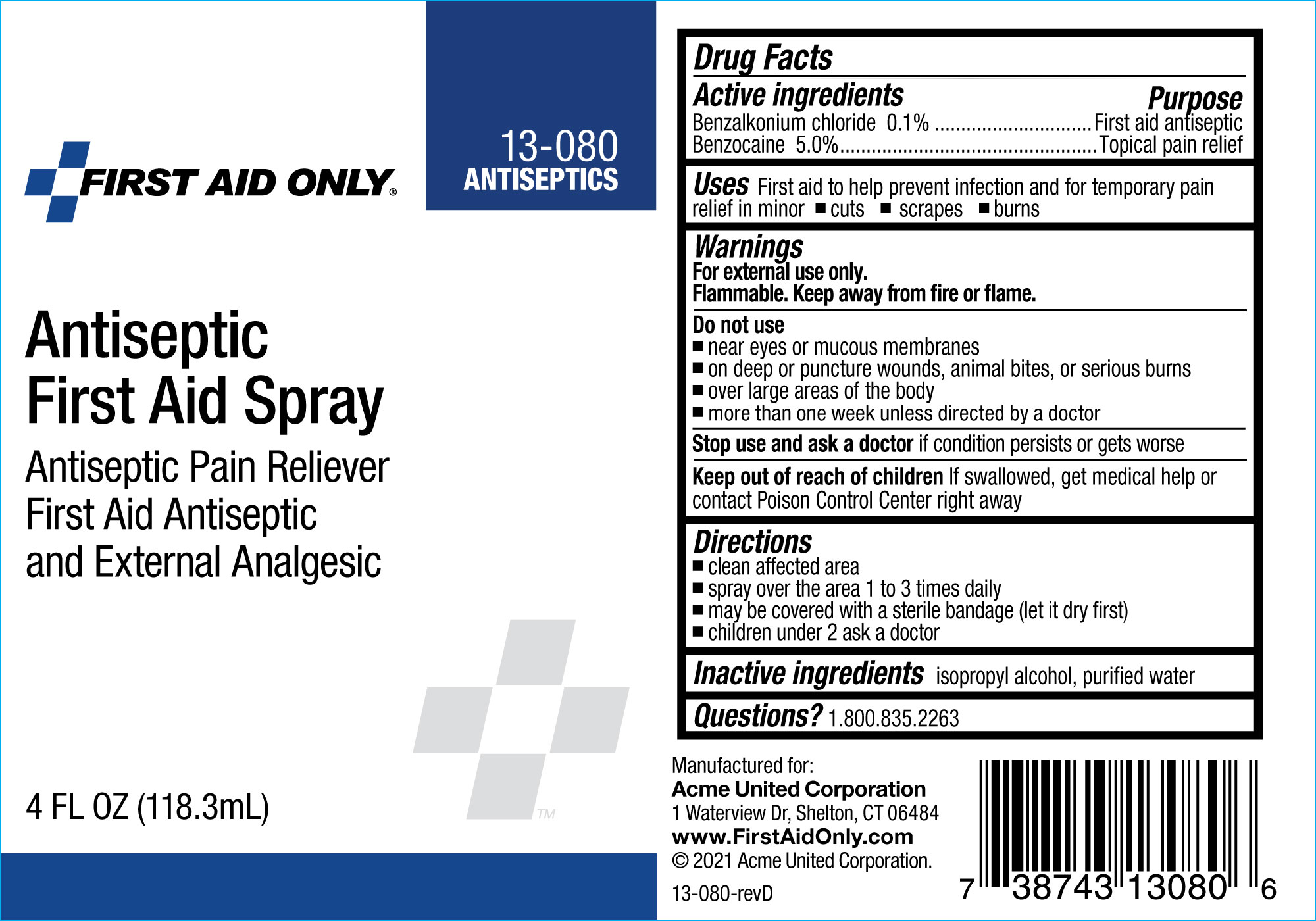 DRUG LABEL: First Aid Only Antiseptic First Aid
NDC: 0924-0938 | Form: SPRAY
Manufacturer: Acme United Corporation
Category: otc | Type: HUMAN OTC DRUG LABEL
Date: 20250523

ACTIVE INGREDIENTS: BENZOCAINE 50 mg/1 g; BENZALKONIUM CHLORIDE 1 mg/1 g
INACTIVE INGREDIENTS: WATER

First Aid Only Antiseptic First Aid Spray

Drug Facts

Benzalkonium Chloride 0.1% Purpose First Aid Antiseptic

Benzocaine 5.0% Purpose Topical Pain Relief

ACTIVE INGREDIENT

Benzalkonium Chloride 0.1% Purpose First Aid Antiseptic

Benzocaine 5.0% Purpose Topical Pain Relief

Uses

First Aid to help prevent infection and for temporary pain relief in minor cuts, scrapes, burns.

clean affected area
spray over the area 1 to 3 times daily
may be covered with a sterile bandage (let it dry first)
children under 2 ask a doctor

Do Not Use

•near eyes or mucous membranes

•on deep or puncture wounds, animal bites, or serious burns

•Over large areas of the body

•More than one week unless directed by a doctor.

Stop use and ask a doctor if condition persists or gets worse

KEEP OUT OF REACH OF CHILDREN

Keep out of the reach of children If swallowed, get medical help or contact Poison Control Center right away

Directions

•Clean affected area

•Spray over the area 1 to 3 times daily

•May be covered bya sterile bandage (let it dry first)

Children uner 2 ask a doctor

Inactive Ingredients

isopropyl alcohol, purified water

Questions? 1.800.835.2263

DOSAGE AND ADMINISTRATION

clean affected area
spray over the area 1 to 3 times daily
may be covered with a sterile bandage (let it dry first)
children under 2 ask a doctor